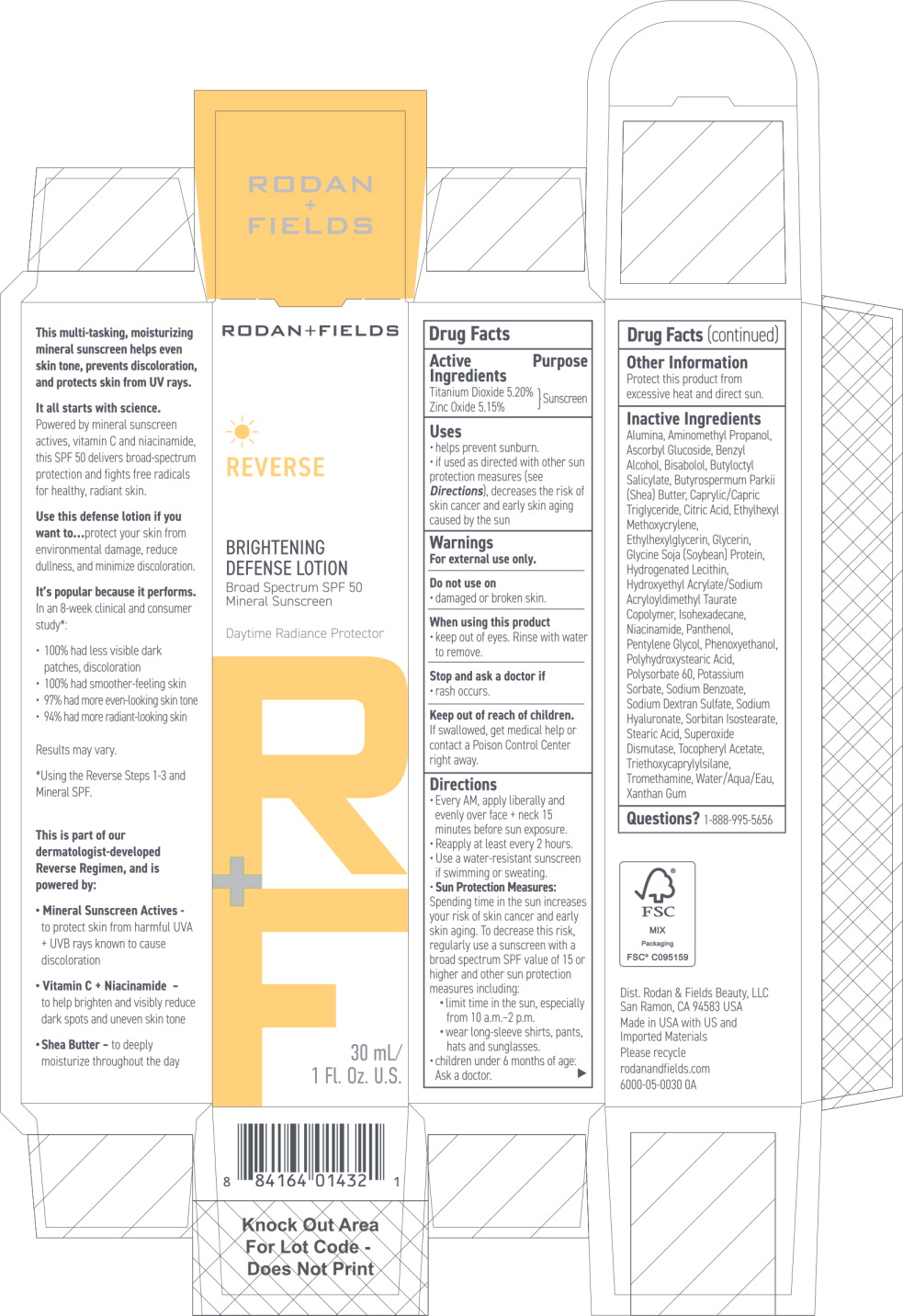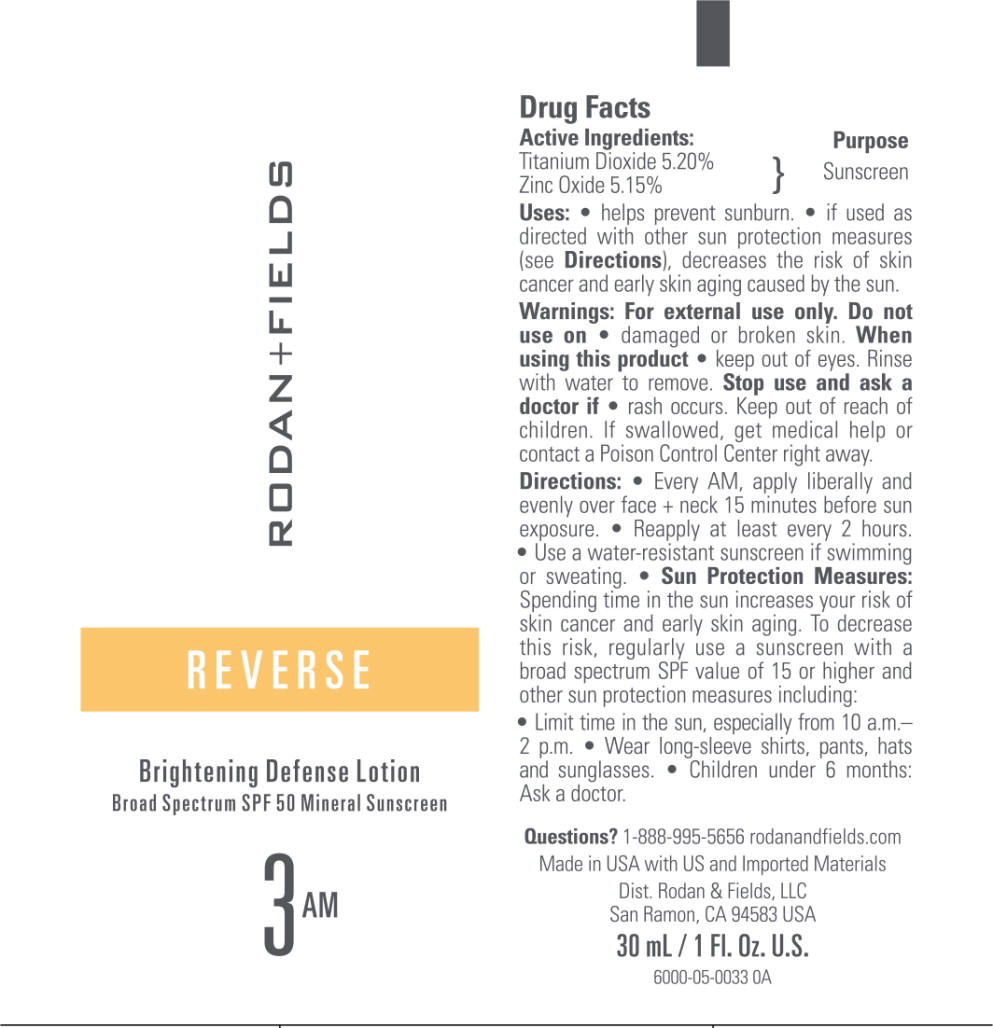 DRUG LABEL: Rodan and Fields Reverse Brightening Defense Broad Spectrum SPF 50 Mineral Sunscreen
NDC: 14222-3001 | Form: LOTION
Manufacturer: Rodan & Fields Beauty, LLC
Category: otc | Type: HUMAN OTC DRUG LABEL
Date: 20250606

ACTIVE INGREDIENTS: Titanium Dioxide 5.2 g/100 mL; Zinc Oxide 5.15 g/100 mL
INACTIVE INGREDIENTS: ALUMINUM OXIDE; AMINOMETHYLPROPANOL; ASCORBYL GLUCOSIDE; BENZYL ALCOHOL; LEVOMENOL; BUTYLOCTYL SALICYLATE; SHEA BUTTER; MEDIUM-CHAIN TRIGLYCERIDES; CITRIC ACID MONOHYDRATE; ETHYLHEXYL METHOXYCRYLENE; ETHYLHEXYLGLYCERIN; GLYCERIN; SOY PROTEIN; HYDROGENATED SOYBEAN LECITHIN; HYDROXYETHYL ACRYLATE/SODIUM ACRYLOYLDIMETHYL TAURATE COPOLYMER (100000 MPA.S AT 1.5%); ISOHEXADECANE; NIACINAMIDE; PANTHENOL; PENTYLENE GLYCOL; PHENOXYETHANOL; POLYHYDROXYSTEARIC ACID (2300 MW); POLYSORBATE 60; POTASSIUM SORBATE; SODIUM BENZOATE; HYALURONATE SODIUM; SORBITAN ISOSTEARATE; STEARIC ACID; SUPEROXIDE DISMUTASE (SACCHAROMYCES CEREVISIAE); .ALPHA.-TOCOPHEROL ACETATE; TRIETHOXYCAPRYLYLSILANE; TROMETHAMINE; WATER; XANTHAN GUM

Drug Facts

Active Ingredients

Titanium Dioxide 5.20%

Zinc Oxide 5.15%

Purpose

Sunscreen

Uses

- helps prevent sunburn.
- if used as directed with other sun protection measures (see Directions), decreases the risk of skin cancer and early skin aging caused by the sun.

Warnings

For external use only.

Do not use on

- damaged or broken skin.

When using this product

- keep out of eyes. Rinse with water to remove.

Stop use and ask a doctor if

- rash occurs.

Keep out of reach of children.

If swallowed, get medical help or contact a Poison Control Center right away.

Directions

- Every AM, apply liberally and evenly over face + neck 15 minutes before sun exposure.
- Reapply at least every 2 hours.
- Use a water-resistant sunscreen if swimming or sweating.
- Sun Protection Measures:
  Spending time in the sun increases your risk of skin cancer and early skin aging. To decrease this risk, regularly use a sunscreen with a broad spectrum SPF value of 15 or higher and other sun protection measures including:
  - limit time in the sun, especially from 10 a.m- 2 p.m.
  - wear long-sleeve shirts, pants, hats and sunglasses.
- children under 6 months: Ask a doctor.

Other Information

Protect this product from excessive heat and direct sun.

Inactive Ingredients

Alumina, Aminomethyl Propanol, Ascorbyl Glucoside, Benzyl Alcohol, Bisabolol, Butyloctyl Salicylate, Butyrospermum Parkii (Shea) Butter, Caprylic/Capric Triglyceride, Citric Acid, Ethylhexyl Methoxycrylene, Ethylhexylglycerin, Glycerin, Glycine Soja (Soybean) Protein, Hydrogenated Lecithin, Hydroxyethyl Acrylate/Sodium Acryloyldimethyl Taurate Copolymer, Isohexadecane, Niacinamide, Panthenol, Pentylene Glycol, Phenoxyethanol, Polyhydroxystearic Acid, Polysorbate 60, Potassium Sorbate, Sodium Benzoate, Sodium Dextran Sulfate, Sodium Hyaluronate, Sorbitan Isostearate, Stearic Acid, Superoxide Dismutase, Tocopheryl Acetate, Triethoxycaprylylsilane, Tromethamine, Water/Aqua/Eau, Xanthan Gum

Questions?

1-888-995-5656

Principal Display Panel - 30 mL Carton Label

RODAN+FIELDS

REVERSE

BRIGHTENING
DEFENSE LOTION

Broad Spectrum SPF 50
Mineral Sunscreen

Daytime Radiance Protector

30 mL/
1. Fl. Oz. U.S.

Principal Display Panel - 30 mL Tube Label

RODAN+FIELDS

REVERSE

Brightening Defense Lotion

Broad Spectrum SPF 50 Mineral Sunscreen

3AM